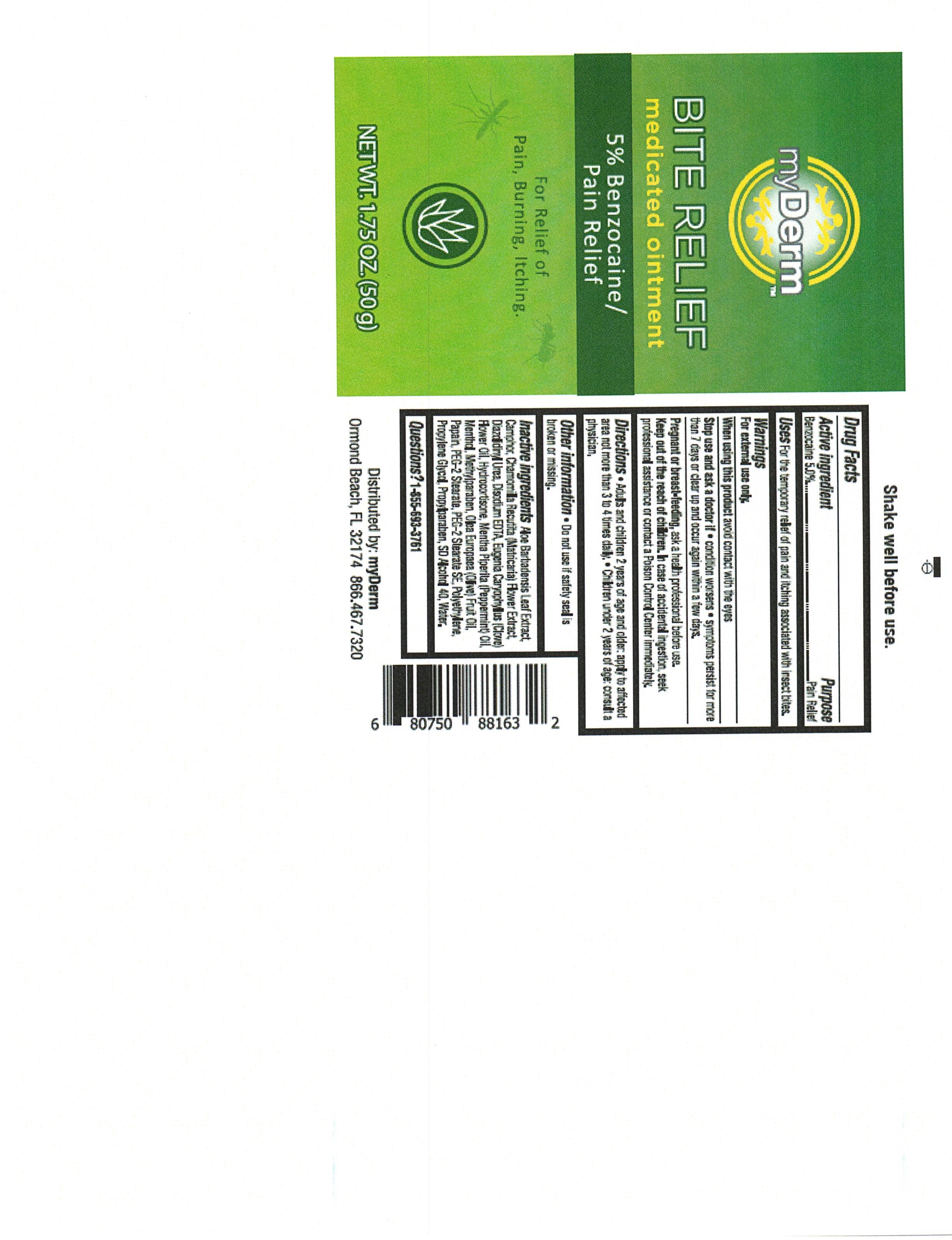 DRUG LABEL: MyDerm Bite Relief
NDC: 72667-019 | Form: OINTMENT
Manufacturer: Inspec Solutions LLC.
Category: otc | Type: HUMAN OTC DRUG LABEL
Date: 20250131

ACTIVE INGREDIENTS: BENZOCAINE 5 g/100 g
INACTIVE INGREDIENTS: PEG-8 DIMETHICONE; PEPPERMINT OIL; PROPYLPARABEN; WATER; PEG-2 STEARATE; EDETATE DISODIUM; CAMPHOR (NATURAL); MATRICARIA CHAMOMILLA FLOWERING TOP OIL; CLOVE OIL; PROPYLENE GLYCOL 1,2-DISTEARATE; OLEA EUROPAEA (OLIVE) OIL UNSAPONIFIABLES; ALOE; METHYLPARABEN; DIAZOLIDINYL UREA; ALCOHOL; MEDIUM DENSITY POLYETHYLENE; MENTHOL; HYDROCORTISONE

MyDerm Bite Relief Mediocated Ointment

Active Ingredient:

Benzocaine - 5.0%

PURPOSE

Benzocaine - 10.0% ............Pain Relief

INDICATIONS AND USAGE

Temporary relief of pain and itching associated with insect bites

WARNINGS

For external use only

When using this product • avoid contact with the eye

Stop use and ask a doctor if • condition worsens, or if symptoms persist for more than 7 days or clear up and occur again within a few days.

Keep out of reach of children. If swallowed, get medical help or contact a Poison Control Center right away.

DOSAGE AND ADMINISTRATION

Direction Adults and children 2 years of age and older: Apply to affected area not more than 3 to 4 times daily.

Children under 2 years of age: consult a physician

INACTIVE INGREDIENT

Aloe Barbadensis Leaf Extract

Camphor

Chamomilla Recutita (Matricaria) Flower Extract

Diazolidinyl Urea

Disodium EDTA

Eugenia Caryophyllus (Clove) Flower Oil

Hydrocortisone

Inactive Ingredients:

Mentha Piperita (Peppermint) Oil

Menthol

Methylparaben

Olea Europaea (Olive) Fruit Oil

Papain

PEG-2 Stearate

PEG-2 Stearate SE

Polyethylene

Propylene Glycol

Propylparaben

SD Alcohol 40

Water